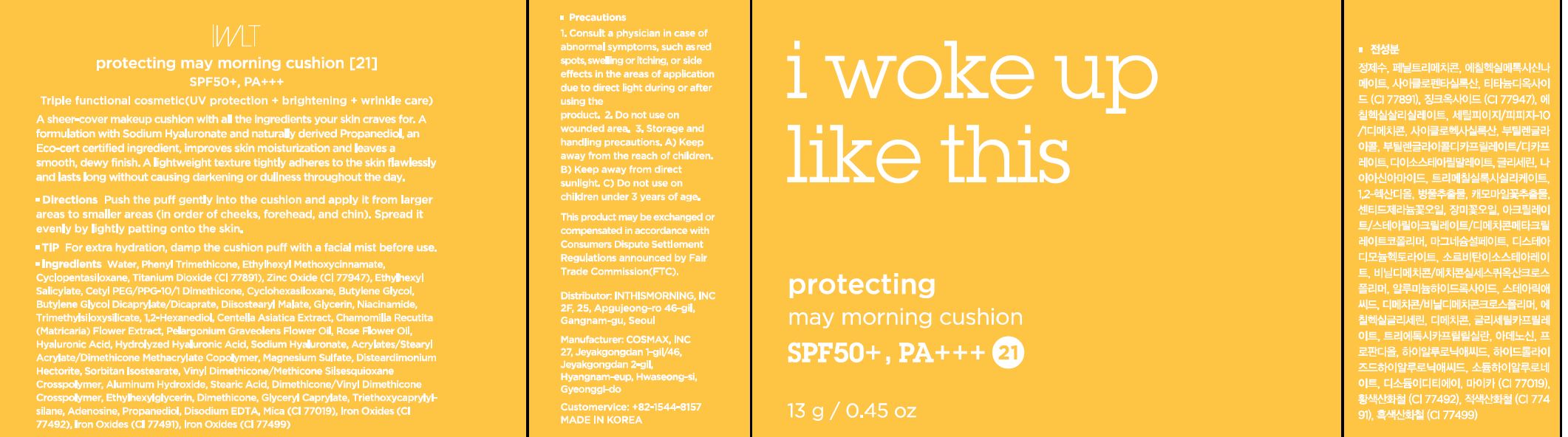 DRUG LABEL: Protecting may morning cushion 21
NDC: 71217-0057 | Form: POWDER
Manufacturer: inthismorning co ltd
Category: otc | Type: HUMAN OTC DRUG LABEL
Date: 20230205

ACTIVE INGREDIENTS: LINALOOL, (+/-)- 0.0028142856 g/100 g; .BETA.-CITRONELLOL, (R)- 0.03018988 g/100 g; GERANIOL 0.007430248 g/100 g
INACTIVE INGREDIENTS: WATER; GLYCERIN

Drug Facts

ACTIVE INGREDIENT

citronellol, geraniol, linalool

INACTIVE INGREDIENT

Water
Phenyl Trimethicone
Ethylhexyl Methoxycinnamate
Cyclopentasiloxane
Titanium Dioxide (CI 77891)
Zinc Oxide (CI 77947)
Ethylhexyl Salicylate
Cetyl PEG/PPG-10/1 Dimethicone
Cyclohexasiloxane
Butylene Glycol
Butylene Glycol Dicaprylate/Dicaprate
Diisostearyl Malate
Glycerin
Niacinamide
Trimethylsiloxysilicate
1,2-Hexanediol
Acrylates/Stearyl Acrylate/Dimethicone Methacrylate Copolymer
Magnesium Sulfate
Mica (CI 77019)
Disteardimonium Hectorite
Sorbitan Isostearate
Vinyl Dimethicone/Methicone Silsesquioxane Crosspolymer
Aluminum Hydroxide
Iron Oxides (CI 77492)
Stearic Acid
Dimethicone/Vinyl Dimethicone Crosspolymer
Ethylhexylglycerin
Centella Asiatica Extract
Chamomilla Recutita (Matricaria) Flower Extract
Dimethicone
Glyceryl Caprylate
Triethoxycaprylylsilane
Iron Oxides (CI 77491)
Adenosine
Iron Oxides (CI 77499)
Disodium EDTA
Pelargonium Graveolens Flower Oil
Rose Flower Oil
Propanediol
Hyaluronic Acid
Hydrolyzed Hyaluronic Acid
Sodium Hyaluronate

PURPOSE

brightening, wrinkle care

keep out or reach of the children

INDICATIONS AND USAGE

push the puff gently into the cushion and apply it from larger areas to smaller areas

spread it evenly by lishtly patting onto the skin

WARNINGS

This product is for exeternal use only. Do not use for internal use
Storage and handling precautions
If possible, avoid direct sunlight and store in cool and area of low humidity in order to maintain the quality of the product and avoid misuse
Avoid placing the product near fire and store out in reach of children

- consult a physician in case of abnormal symptoms, such as red spots, swelling or itching, or side effects in the areas of application due to direct light during or after using the product

- do not use on wounded area

DOSAGE AND ADMINISTRATION

for external use only